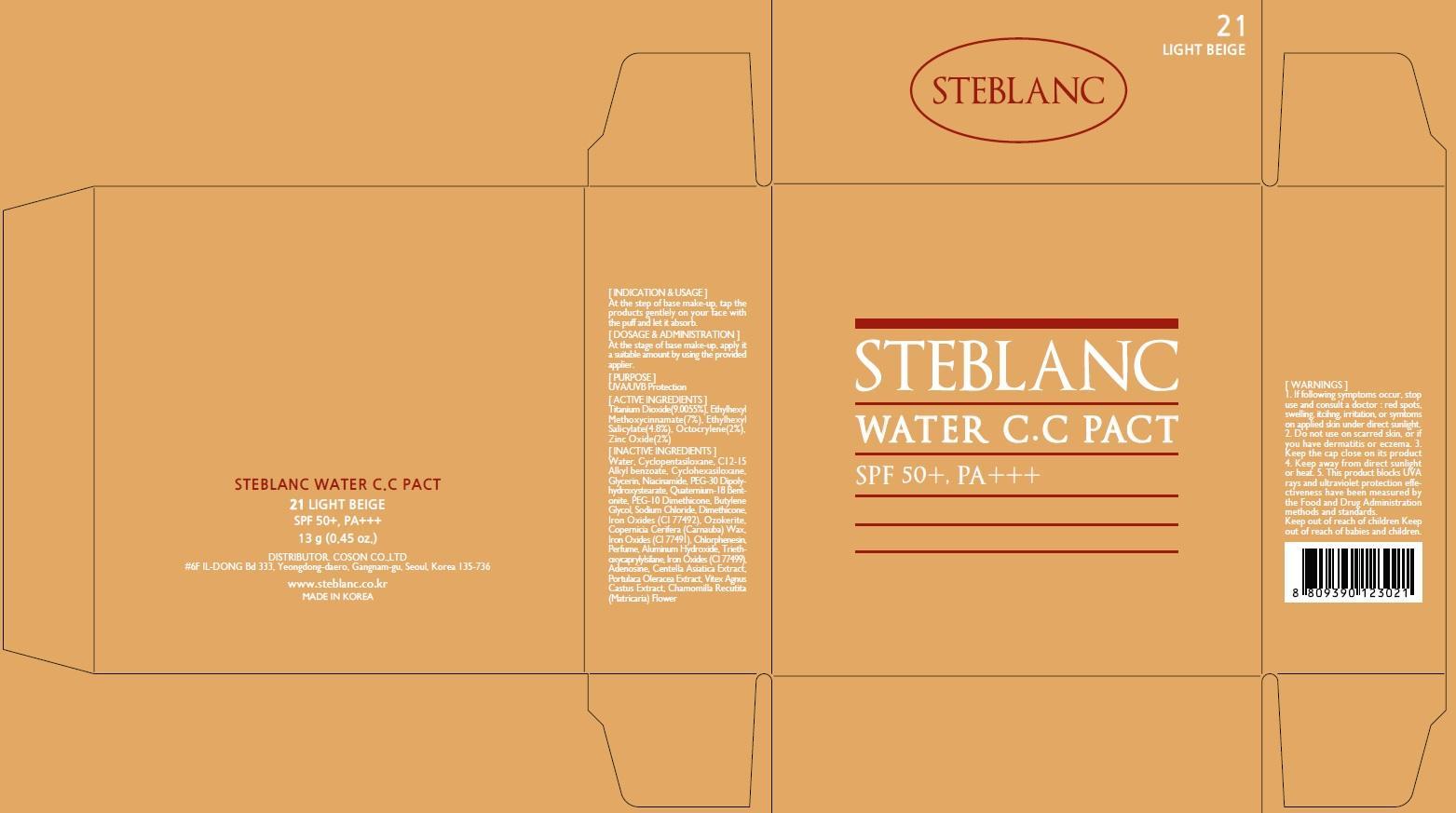 DRUG LABEL: STEBLANC WATER CC PACT
NDC: 62171-050 | Form: POWDER
Manufacturer: Coson Co., Ltd.
Category: otc | Type: HUMAN OTC DRUG LABEL
Date: 20140923

ACTIVE INGREDIENTS: Titanium Dioxide 1.17 g/13 g; Octinoxate 0.91 g/13 g; Octisalate 0.62 g/13 g; Octocrylene 0.26 g/13 g; Zinc Oxide 0.26 g/13 g
INACTIVE INGREDIENTS: Water; C12-15 Alkyl benzoate

ACTIVE INGREDIENT

ACTIVE INGREDIENTS: Titanium Dioxide 9.0055%, Ethylhexyl Methoxycinnamate 7%, Ethylhexyl Salicylate 4.8%, Octocrylene 2%, Zinc Oxide 2%

INACTIVE INGREDIENT

INACTIVE INGREDIENTS:
Water, Cyclopentasiloxane, C12-15 Alkyl benzoate, Cyclohexasiloxane, Glycerin, Niacinamide, PEG-30 Dipolyhydroxystearate, Quaternium-18 Bentonite, PEG-10 Dimethicone, Butylene Glycol, Sodium Chloride, Dimethicone, Iron Oxides (CI 77492), Ozokerite, Copernicia Cerifera (Carnauba) Wax, Iron Oxides (CI 77491), Chlorphenesin, Perfume, Aluminum Hydroxide, Triethoxycaprylylsilane, Iron Oxides (CI 77499), Adenosine, Centella Asiatica Extract, Portulaca Oleracea Extract, Vitex Agnus Castus Extract, Chamomilla Recutita (Matricaria) Flower

PURPOSE

PURPOSE: UVA/UVB Protection

WARNINGS

1. If following symptoms occur, stop use and consult a doctor: red spots, swelling, itcihng, irritation, or symtoms on applied skin under direct sunlight.
2. Do not use on scarred skin, or if you have dermatitis or eczema
3. Keep the cap close on its product
4. Keep away from direct sunlight or heat.
5. This product blocks UVA rays and ultraviolet protection effectiveness have been measured by the Food and Drug Administration methods and standards

Keep out of reach of children: Keep out of reach of babies and children

INDICATIONS & USAGE

INDICATION & USAGE:
At the step of base make-up, tap the products gentlely on your face with the puff and let it absorb.

DOSAGE & ADMINISTRATION

At the stage of base make-up, apply it a suitable amount by using the provided applier.